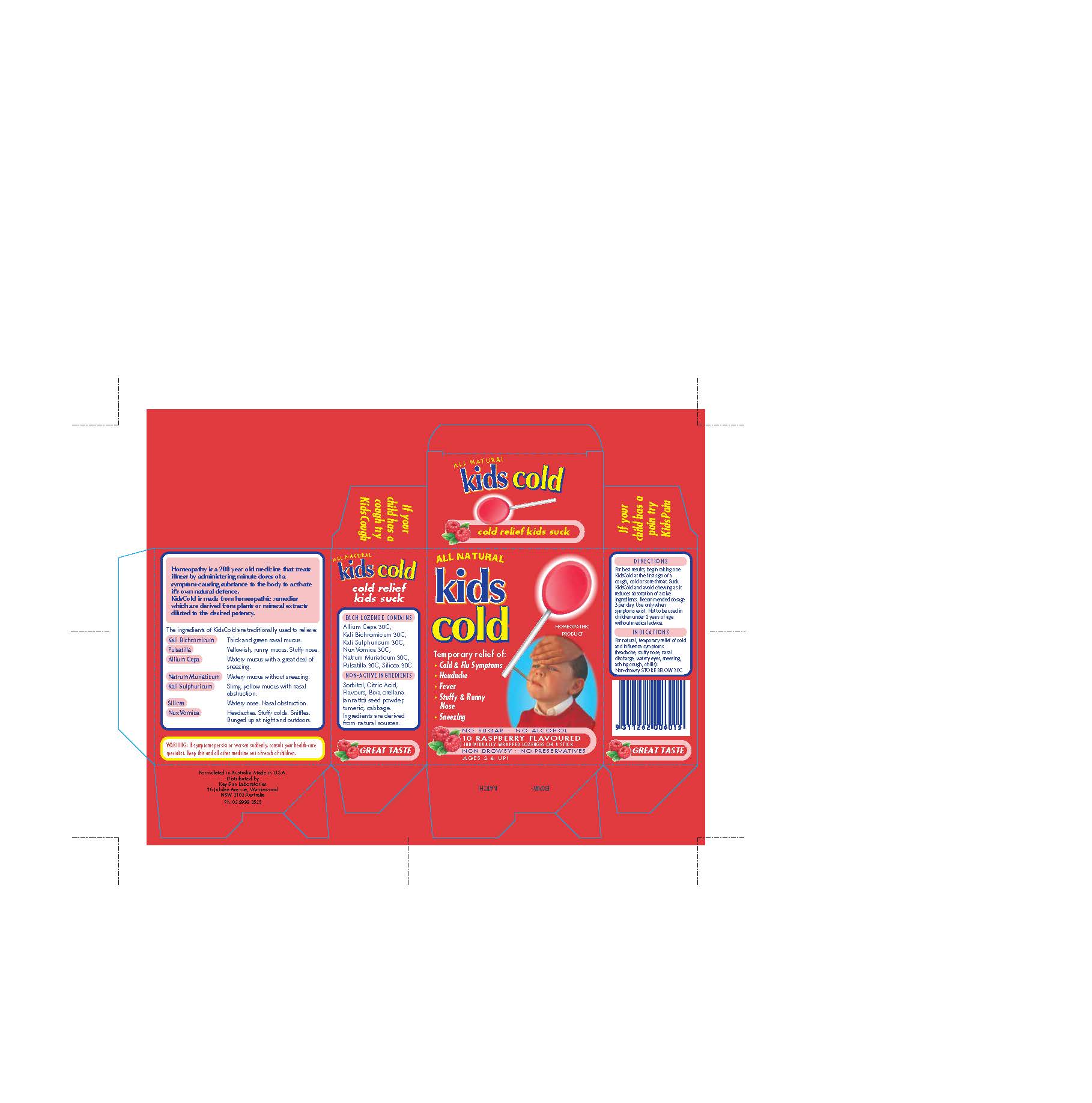 DRUG LABEL: kids cold
                
NDC: 76509-200 | Form: LOZENGE
Manufacturer: Natures Investment Holdings Pty Ltd dba Maxrelief USA
Category: homeopathic | Type: HUMAN OTC DRUG LABEL
Date: 20140503

ACTIVE INGREDIENTS: ONION 30 [hp_X]/1 1; POTASSIUM DICHROMATE 30 [hp_X]/1 1; POTASSIUM SULFATE 30 [hp_X]/1 1; STRYCHNOS NUX-VOMICA SEED 30 [hp_X]/1 1; SODIUM CHLORIDE 30 [hp_X]/1 1; PULSATILLA VULGARIS 30 [hp_X]/1 1; SILICON DIOXIDE 30 [hp_X]/1 1
INACTIVE INGREDIENTS: SORBITOL; CITRIC ACID MONOHYDRATE; BIXA ORELLANA SEED; TURMERIC; CABBAGE

Homeopathic Drug Facts

INACTIVE INGREDIENT

Non-Active Ingredients

Sorbitol, Citric Acid,

Flavours, Bix orellana

(annato) seed powder,

tumeric, cabbage

Ingredients are derived

from natural sources

ACTIVE INGREDIENT

Each Lozenge contains:

Allium Cepa 30C,

Kali Bichromium 30C,

Kali Sulphericum 30C,

Nux Vomica 30C,

Natrum Muriaticum 30C,

Pulsatilla 30C,

Silicea 30C

PURPOSE

Indications

For natural, temporary relief of

cold and influenza symptoms (headache,

stuffy nose, nasal discharge, watery eyes,

sneezing, aching cough, chills)

WARNINGS

Warning: If symptoms persist or worsen suddenly, consult your health-care

specialist.

KEEP OUT OF REACH OF CHILDREN

Keep this and all other medication out of reach of children.

Directions:

For best results, begin taking one

KidsCold at the first sign of a cough, cold or sore

throat. Suck KidsCold and avoid chewing as it reduces

absorption of active ingredients. Recommended dosage

3 per day. Use only when symptoms exist. Not to be used

in children under 2 years of age without

medical advice.

Indications

For natural temporary relief of

cold and influenze symptoms (headache,

stuffy nose, nasal discharge, watery eyes

sneezing aching cough, chills)

Non-drowsy.

STORAGE AND HANDLING

STORE BELOW 30C